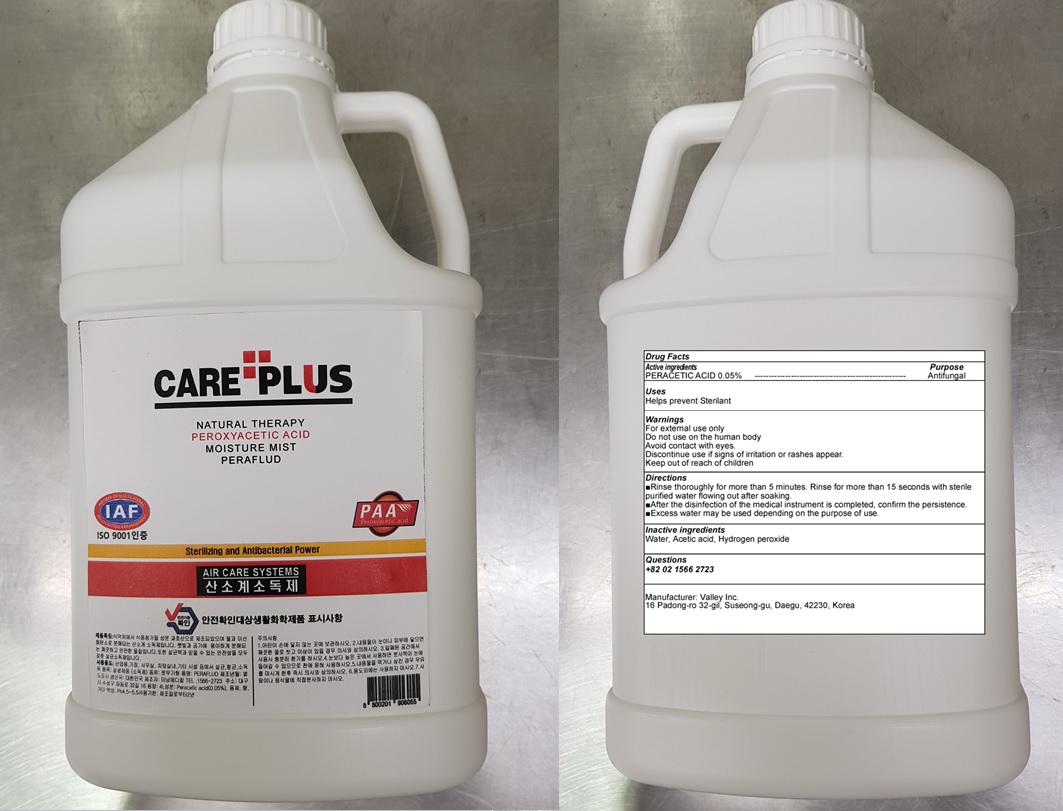 DRUG LABEL: CARE PLUS
NDC: 81803-010 | Form: LIQUID
Manufacturer: Valley Inc.
Category: otc | Type: HUMAN OTC DRUG LABEL
Date: 20210423

ACTIVE INGREDIENTS: PERACETIC ACID 0.05 g/100 mL
INACTIVE INGREDIENTS: Water; Acetic acid; HYDROGEN PEROXIDE

Drug Facts

ACTIVE INGREDIENT

PERACETIC ACID 0.05%

INACTIVE INGREDIENTS

Water, Acetic acid, Hydrogen peroxide

PURPOSE

Antifungal

WARNINGS

For external use only
Do not use on the human body
Avoid contact with eyes.
Discontinue use if signs of irritation or rashes appear.
Keep out of reach of children

Keep out of reach of children

Uses

Helps prevent Sterilant

Directions

■Rinse thoroughly for more than 5 minutes. Rinse for more than 15 seconds with sterile purified water flowing out after soaking.
■After the disinfection of the medical instrument is completed, confirm the persistence.
■Excess water may be used depending on the purpose of use.

Questions

+82 02 1566 2723